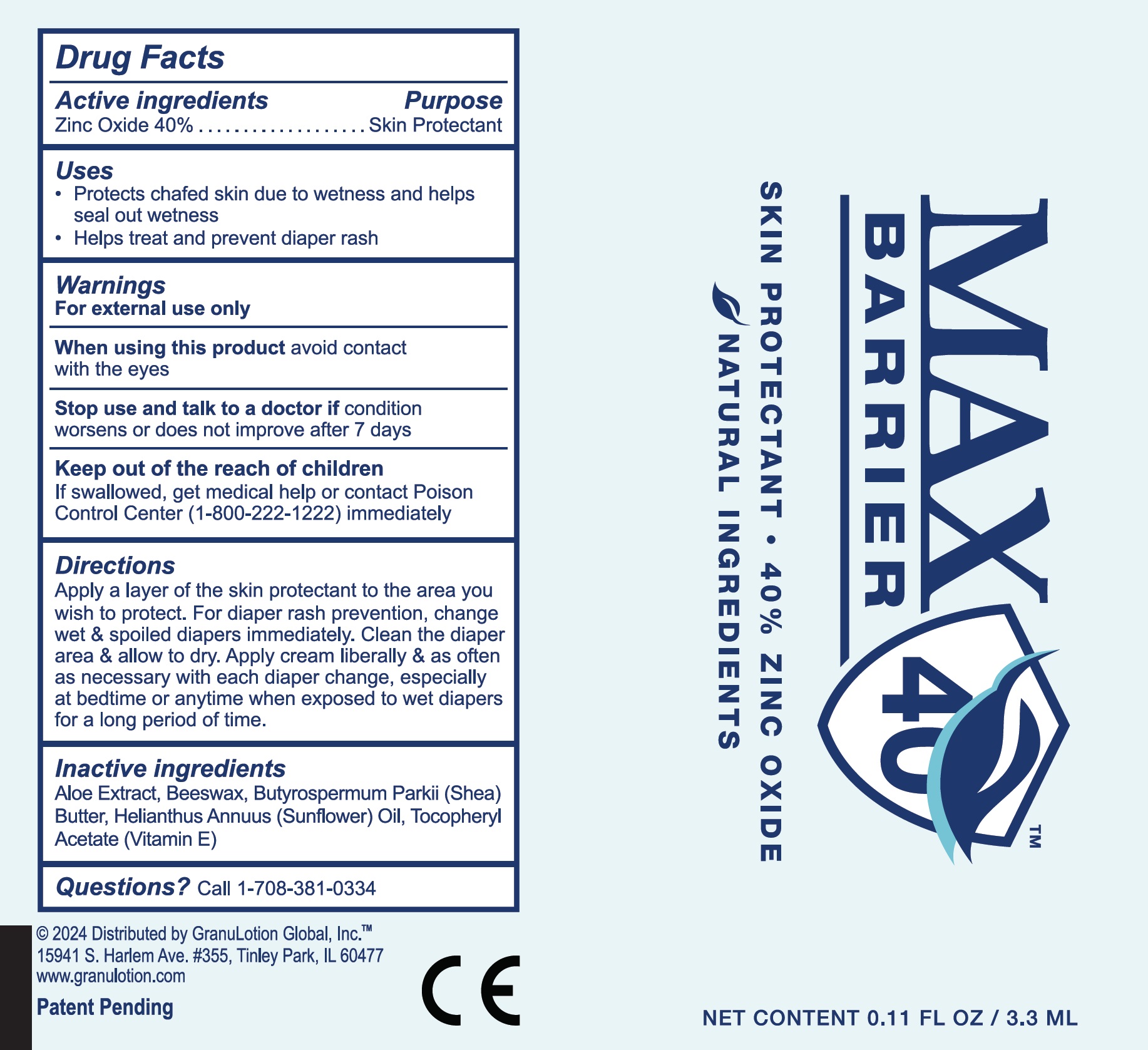 DRUG LABEL: MAX BARRIER Skin Protectant
NDC: 82897-468 | Form: CREAM
Manufacturer: GL HEALTH, INC.
Category: otc | Type: HUMAN OTC DRUG LABEL
Date: 20240226

ACTIVE INGREDIENTS: ZINC OXIDE 400 mg/1 mL
INACTIVE INGREDIENTS: ALOE; YELLOW WAX; SHEA BUTTER; HELIANTHUS ANNUUS FLOWERING TOP; .ALPHA.-TOCOPHEROL

MAX BARRIER Skin Protectant

Active ingredients

Zinc Oxide 40%

Purpose

Skin Protectant

Uses

- Protects chafed skin due to wetness and helps seal out wetness
- Helps treat and prevent diaper rash

Warnings

For external use only

When using this product

avoid contact with the eyes

Stop use and talk to a doctor if

condition worsens or does not improve after 7 days

Keep out of the reach of children

If swallowed, get medical help or contact Poison Control Center (1-800-222-1222) immediately

Directions

Apply a layer of the skin protectant to the area you wish to protect. For diaper rash prevention, change wet & spoiled diapers immediately. Clean the diaper area & allow to dry. Apply cream liberally & as often as necessary with each diaper change, especially at bedtime or anytime when exposed to wet diapers for a long period of time.

Inactive ingredients

Aloe Extract, Beeswax, Butyrospermum Parkii (Shea) Butter, Helianthus Annuus (Sunflower) Oil, Tocopheryl Acetate (Vitamin E)

Questions?

Call 1-708-381-0334